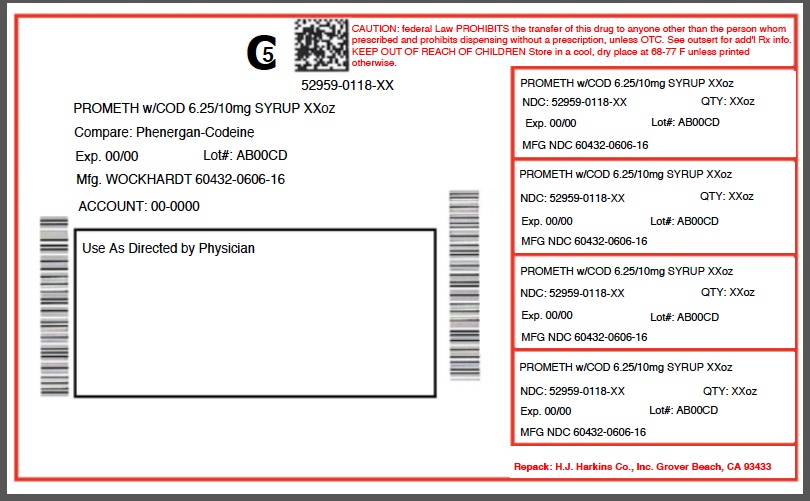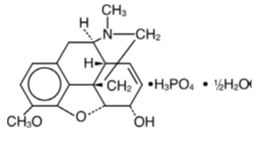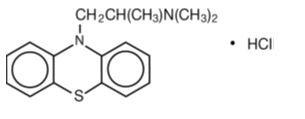 DRUG LABEL: PROMETHAZINE WITH CODEINE
NDC: 52959-118 | Form: SYRUP
Manufacturer: H.J. Harkins Company,Inc.
Category: prescription | Type: HUMAN PRESCRIPTION DRUG LABEL
Date: 20180815
DEA Schedule: CV

ACTIVE INGREDIENTS: PROMETHAZINE HYDROCHLORIDE 6.25 mg/5 mL; CODEINE PHOSPHATE 10 mg/5 mL

0118-04/08

BOXED WARNING

Addiction, Abuse, and Misuse

WARNING: ADDICTION, ABUSE, AND MISUSE; LIFE-THREATENING RESPIRATORY DEPRESSION; ACCIDENTAL INGESTION; ULTRA-RAPID METABOLISM OF CODEINE AND OTHER RISK FACTORS FOR LIFE-THREATENING RESPIRATORY DEPRESSION IN CHILDREN; PROMETHAZINE AND RESPIRATORY DEPRESSION IN CHILDREN; MEDICATION ERRORS; INTERACTIONS WITH DRUGS AFFECTING CYTOCHROME P450 ISOENZYMES; CONCOMITANT USE WITH BENZODIAZEPINES OR OTHER CNS DEPRESSANTS; NEONATAL OPIOID WITHDRAWAL SYNDROME

Addiction, Abuse, and Misuse

Promethazine with Codeine Oral Solution exposes patients and other users to the risks of opioid addiction, abuse, and misuse, which can lead to overdose and death. Reserve Promethazine with Codeine Oral Solution for use in adult patients for whom the benefits of cough suppression are expected to outweigh the risks, and in whom an adequate assessment of the etiology of the cough has been made. Assess each patient's risk prior to prescribing Promethazine with Codeine Oral Solution, prescribe Promethazine with Codeine Oral Solution for the shortest duration that is consistent with individual patient treatment goals, monitor all patients regularly for the development of addition or abuse, and refill only after reevaluation of the need for continued treatment. [see Warnings and Precautions (5.1)]

Life-Threatening Respiratory Depression

Serious, life-threatening, or fatal respiratory depression may occur with use of Promethazine with Codeine Oral Solution. Monitor for respiratory depression, especially during initiation of Promethazine with Codeine Oral Solution therapy or when used in patients at higher risk [see Warnings and Precautions (5.2)].

Accidental Ingestion

Accidental ingestion of even one dose of Promethazine with Codeine Oral Solution, especially by children, can result in a fatal overdose of codeine [see Warnings and Precautions (5.2)].

Ultra-Rapid Metabolism of Codeine and Other Risk Factors for Life-Threatening Respiratory Depression in Children

Life-threatening respiratory depression and death have occurred in children who received codeine. Most of the reported cases occurred following tonsillectomy and/or adenoidectomy, and many of the children had evidence of being an ultra-rapid metabolizer of codeine due to a CYP2D6 polymorphism [see Warnings and Precautions (5.3)]. Promethazine with Codeine Oral Solution is contraindicated in children younger than 12 years of age and in children younger than 18 years of age following tonsillectomy and/or adenoidectomy [see Contraindications (4)]. Avoid the use of Promethazine with Codeine Oral Solution in adolescents 12 to 18 years of age who have other risk factors that may increase their sensitivity to the respiratory depressant effects of codeine.

Promethazine and Respiratory Depression in Children

Postmarketing cases of respiratory depression, including fatalities have been reported with use of promethazine in pediatric patients. Children may be particularly sensitive to the additive respiratory depressant effects when promethazine is combined with other respiratory depressants, including codeine. [see Warnings and Precautions (5.4)].

Risk of Medication Errors

Ensure accuracy when prescribing, dispensing, and administering Promethazine with Codeine Oral Solution. Dosing errors can result in accidental overdose and death. Always use an accurate milliliter measuring device when measuring and administering Promethazine with Codeine Oral Solution [see Dosage and Administration (2.1), Warnings and Precautions (5.7)].

Interactions with Drugs Affecting Cytochrome P450 Isoenzymes

The effects of concomitant use or discontinuation of cytochrome P450 3A4 inducers, 3A4 inhibitors, or 2D6 inhibitors with codeine are complex, requiring careful consideration of the effects on the parent drug, codeine, and the active metabolite, morphine. Avoid the use of Promethazine with Codeine Oral Solution in patients who are taking a CYP3A4 inhibitor, CYP3A4 inducer, or 2D6 inhibitor [see Warnings and Precautions (5.9), Drug Interactions (7.1, 7.2, 7.3)].

Risks from Concomitant Use with Benzodiazepines or Other CNS Depressants

Concomitant use of opioids with benzodiazepines or other central nervous system (CNS) depressants, including alcohol, may result in profound sedation, respiratory depression, coma, and death. Avoid the use of Promethazine with Codeine Oral Solution in patients taking benzodiazepines, other CNS depressants, or alcohol. [see Warnings and Precautions (5.10), Drug Interactions (7.4)].

Neonatal Opioid Withdrawal Syndrome

Promethazine with Codeine Oral Solution is not recommended for use in pregnant women [see Use in Specific Populations (8.1)]. Prolonged use of Promethazine with Codeine Oral Solution during pregnancy can result in neonatal opioid withdrawal syndrome, which may be life-threatening if not recognized and treated, and requires management according to protocols developed by neonatology experts. If Promethazine with Codeine Oral Solution is used for a prolonged period in a pregnant woman, advise the patient of the risk of neonatal opioid withdrawal syndrome and ensure that appropriate treatment will be available [see Warnings and Precautions (5.20)].

INDICATIONS AND USAGE

Promethazine with Codeine Oral Solution is indicated for the temporary relief of coughs and upper respiratory symptoms associated with allergy or the common cold in patients 18 years of age and older.

Important Limitations of Use

- Not indicated for pediatric patients under 18 years of age.
- Contraindicated in pediatric patients under 12 years of age.
- Contraindicated in pediatric patients 12 to 18 years of age after tonsillectomy or adenoidectomy.
- Because of the risks of addiction, abuse, and misuse with opioids, even at recommended doses, reserve Promethazine with Codeine Oral Solution for use in adult patients for whom the benefits of cough suppression are expected to outweigh the risks, and in whom an adequate assessment of the etiology of the cough has been made.

2.1 Important Dosage and Administration Instructions

Administer Promethazine with Codeine Oral Solution by the oral route only.

Always use an accurate milliliter measuring device when administering Promethazine with Codeine Oral Solution to ensure that the dose is measured and administered accurately. A household teaspoon is not an accurate measuring device and could lead to overdosage. For prescriptions where a measuring device is not provided, a pharmacist can provide an appropriate measuring device and can provide instructions for measuring the correct dose. Do not overfill. Rinse the measuring device with water after each use.

Advise patients not to increase the dose or dosing frequency of Promethazine with Codeine Oral Solution because serious adverse events such as respiratory depression may occur with overdosage. The dosage of Promethazine with Codeine Oral Solution should not be increased if cough fails to respond; an unresponsive cough should be reevaluated for possible underlying pathology.

2.2 Recommended Dosage

Adults 18 years of age and older: 5 mL every 4 to 6 hours as needed, not to exceed 6 doses (30 mL) in 24 hours.

2.3 Monitoring, Maintenance, and Discontinuation of Therapy

Prescribe Promethazine with Codeine Oral Solution for the shortest duration that is consistent with individual patient treatment goals.

Monitor patients closely for respiratory depression, especially within the first 24-72 hours of initiating therapy.

Reevaluate patients with unresponsive cough in 5 days or sooner for possible underlying pathology, such as foreign body or lower respiratory tract disease. If a patient requires a refill, reevaluate the cause of the cough and assess the need for continued treatment with Promethazine with Codeine Oral Solution, the relative incidence of adverse reactions, and the development of addiction, abuse, or misuse.

Do not abruptly discontinue Promethazine with Codeine Oral Solution in a physically-dependent patient. When a patient who has been taking Promethazine with Codeine Oral Solution regularly and may be physically dependent no longer requires therapy with Promethazine with Codeine Oral Solution, taper the dose gradually, by 25% to 50% every 2 to 4 days, while monitoring carefully for signs and symptoms of withdrawal. If the patient develops these signs or symptoms, raise the dose to the previous level and taper more slowly, either by increasing the interval between decreases, decreasing the amount of change in dose, or both.

DOSAGE FORMS AND STRENGTHS

Oral solution: Each 5 mL contains codeine phosphate, 10 mg and promethazine hydrochloride 6.25 mg, in a flavored syrup base.

CONTRAINDICATIONS

Promethazine with Codeine Oral Solution is contraindicated for:
All children younger than 12 years of age [see WARNINGS AND PRECAUTIONS (5.2, 5.3, 5.5), USE IN SPECIFIC POPULATIONS (8.4) ].
Postoperative pain management in children younger than 18 years of age following tonsillectomy and/or adenoidectomy [see WARNINGS AND PRECAUTIONS (5.2, 5.3) ].
Promethazine with Codeine Oral Solution is also contraindicated in patients with:
Significant respiratory depression [see WARNINGS AND PRECAUTIONS (5.2) ].
Acute or severe bronchial asthma in an unmonitored setting or in the absence of resuscitative equipment [see WARNINGS AND PRECAUTIONS (5.6) ].
Known or suspected gastrointestinal obstruction, including paralytic ileus [SEE WARNINGS AND PRECAUTIONS (5.11) ].
A history of an idiosyncratic reaction to promethazine or to other phenothiazines [SEE WARNINGS AND PRECAUTIONS (5.14) ].
Concurrent use of monoamine oxidase inhibitors (MAOIs) or use of MAOIs within 14 days [see WARNINGS AND PRECAUTIONS (5.16), DRUG INTERACTIONS (7.6) ].
Hypersensitivity to codeine, promethazine, or any of the inactive ingredients in Promethazine with Codeine Oral Solution [SEE ADVERSE REACTIONS (6) ]. Persons known to be hypersensitive to certain other opioids may exhibit cross-reactivity to codeine.

WARNINGS AND PRECAUTIONS

5.1 Addiction, Abuse, and Misuse

Promethazine with Codeine Oral Solution contains codeine, a Schedule V controlled substance. As an opioid, Promethazine with Codeine Oral Solution exposes users to the risks of addiction, abuse, and misuse [see DRUG ABUSE AND DEPENDENCE (9)], which can lead to overdose and death [seeOVERDOSAGE (10)]. Reserve Promethazine with Codeine Oral Solution for use in adult patients for whom the benefits of cough suppression are expected to outweigh the risks, and in whom an adequate assessment of the etiology of the cough has been made. Assess each patient's risk prior to prescribing Promethazine with Codeine Oral Solution, prescribe Promethazine with Codeine Oral Solution for the shortest duration that is consistent with individual patient treatment goals, monitor all patients regularly for the development of addiction or abuse, and refill only after reevaluation of the need for continued treatment.

Although the risk of addiction in any individual is unknown, it can occur in patients appropriately prescribed Promethazine with Codeine Oral Solution. Addiction can occur at recommended dosages and if the drug is misused or abused. Risks are increased in patients with a personal or family history of substance abuse (including drug or alcohol abuse or addiction) or mental illness (e.g., major depression).

Opioids are sought by drug abusers and people with addiction disorders and are subject to criminal diversion. Consider these risks when prescribing or dispensing Promethazine with Codeine Oral Solution. Strategies to reduce these risks include prescribing the drug in the smallest appropriate quantity and advising the patient on the proper disposal of unused drug [see PATIENT COUNSELING INFORMATION (17)]. Contact local state professional licensing board or state controlled substances authority for information on how to prevent and detect abuse or diversion of this product.

5.2 Life-Threatening Respiratory Depression

Serious, life-threatening, or fatal respiratory depression has been reported with the use of opioids, including codeine, one of the active ingredients in Promethazine with Codeine Oral Solution. Codeine produces dose-related respiratory depression by directly acting on the brain stem respiratory center that controls respiratory rhythm and may produce irregular and periodic breathing. Codeine is subject to variability in metabolism based upon CYP2D6 genotype, which can lead to an increased exposure to the active metabolite morphine [see WARNINGS AND PRECAUTIONS (5.3)]. Promethazine exerts a depressant effect on the respiratory center that is independent of and additive to that of other respiratory depressants, including codeine [see WARNINGS AND PRECAUTIONS (5.4)]. Respiratory depression, if not immediately recognized and treated, may lead to respiratory arrest and death. Management of respiratory depression includes discontinuation of Promethazine with Codeine Oral Solution, close observation, supportive measures, and use of opioid antagonists (e.g. naloxone), depending on the patient's clinical status [see OVERDOSAGE (10)]. Carbon dioxide (CO2) retention from opioid-induced respiratory depression can exacerbate the sedating effects of opioids.

While serious, life-threatening, or fatal respiratory depression can occur at any time during the use of Promethazine with Codeine Oral Solution, the risk is greatest during the initiation of therapy, when Promethazine with Codeine Oral Solution is used concomitantly with other drugs that may cause respiratory depression [see WARNINGS AND PRECAUTIONS (5.10)], in patients with chronic pulmonary disease or decreased respiratory reserve, and in patients with altered pharmacokinetics or altered clearance (e.g. elderly, cachectic, or debilitated patients) [see WARNINGS AND PRECAUTIONS (5.6)].

To reduce the risk of respiratory depression, proper dosing of Promethazine with Codeine Oral Solution is essential [see DOSAGE AND ADMINISTRATION (2.1), WARNINGS AND PRECAUTIONS (5.7)]. Monitor patients closely, especially within the first 24-72 hours of initiating therapy or when used in patients at higher risk.

Overdose of codeine in adults has been associated with fatal respiratory depression, and the use of codeine in children younger than 12 years of age has been associated with fatal respiratory depression when used as recommended [see WARNINGS AND PRECAUTIONS (5.3)]. Accidental ingestion of even one dose of Promethazine with Codeine Oral Solution, especially by children, can result in respiratory depression and death.

5.3 Ultra-Rapid Metabolism of Codeine and Other Risk Factors for Life-Threatening Respiratory Depression in Children

Life-threatening respiratory depression and death have occurred in children who received codeine. Codeine is subject to variability in metabolism based upon CYP2D6 genotype (described below), which can lead to an increased exposure to the active metabolite morphine. Based upon post-marketing reports, children younger than 12 years old appear to be more susceptible to the respiratory depressant effects of codeine, particularly if there are risk factors for respiratory depression. For example, many reported cases of death occurred in the post-operative period following tonsillectomy and/or adenoidectomy, and many of the children had evidence of being ultra-rapid metabolizers of codeine. Furthermore, children with obstructive sleep apnea who are treated with codeine for post-tonsillectomy and/or adenoidectomy pain may be particularly sensitive to its respiratory depressant effect. Because of the risk of life-threatening respiratory depression and death:

Promethazine with Codeine Oral Solution is contraindicated in all children younger than 12 years of age [see CONTRAINDICATIONS (4) ].
Promethazine with Codeine Oral Solution is contraindicated for post-operative management in pediatric patients younger than 18 years of age following tonsillectomy and/or adenoidectomy [see CONTRAINDICATIONS (4) ].
Avoid the use of Promethazine with Codeine Oral Solution in adolescents 12 to 18 years of age who have other risk factors that may increase their sensitivity to the respiratory depressant effects of codeine. Risk factors include conditions associated with hypoventilation, such as postoperative status, obstructive sleep apnea, obesity, severe pulmonary disease, neuromuscular disease, and concomitant use of other medications that cause respiratory depression. [see WARNINGS AND PRECAUTIONS (5.10), USE IN SPECIFIC POPULATIONS (8.4) ]
Healthcare providers should choose the lowest effective dose for the shortest period of time and inform patients and caregivers about these risks and the signs of morphine overdose [see WARNINGS AND PRECAUTIONS (5.1), OVERDOSAGE (10) ].

Lactation

At least one death was reported in a nursing infant who was exposed to high levels of morphine in breast milk because the mother was an ultra-rapid metabolizer of codeine. Breastfeeding is not recommended during treatment with Promethazine with Codeine Oral Solution [see USE IN SPECIFIC POPULATIONS (8.2)].

CYP2D6 Genetic Variability: Ultra-Rapid Metabolizers

Some individuals may be ultra-rapid metabolizers because of a specific CYP2D6 genotype (e.g., gene duplications denoted as *1/*1xN or *1/*2xN). The prevalence of this CYP2D6 phenotype varies widely and has been estimated at 1 to 10% for Whites (European, North American), 3 to 4% for Blacks (African Americans), 1 to 2% for East Asians (Chinese, Japanese, Korean), and may be greater than 10% in certain ethnic groups (i.e., Oceanian, Northern African, Middle Eastern, Ashkenazi Jews, Puerto Rican). These individuals convert codeine into its active metabolite, morphine, more rapidly and completely than other people. This rapid conversion results in higher than expected serum morphine levels. Even at labeled dosage regimens, individuals who are ultra-rapid metabolizers may have life-threatening or fatal respiratory depression or experience signs of overdose (such as extreme sleepiness, confusion, or shallow breathing) [see OVERDOSAGE (10)]. Therefore, individuals who are ultra-rapid metabolizers should not use Promethazine with Codeine Oral Solution.

5.4 Promethazine and Respiratory Depression

Children

Postmarketing cases of respiratory depression, including fatalities, have been reported with use of promethazine in pediatric patients. Concomitant administration with other respiratory depressants may increase the risk of respiratory depression. Children may be particularly sensitive to the additive respiratory depressant effects when promethazine is combined with other respiratory depressants, including codeine [see WARNINGS AND PRECAUTIONS (5.3, 5.5, 5.10)].

Excessively large dosages of antihistamines, including promethazine hydrochloride, in pediatric patients may cause sudden death [see OVERDOSAGE (10)].

Concomitant Conditions and Other Risk Factors

Avoid use of promethazine in patients at risk for respiratory depression. Risk factors include conditions associated with hypoventilation, such as postoperative status, obstructive sleep apnea, obesity, severe pulmonary disease, neuromuscular disease, and concomitant use of other medications that cause respiratory depression [see WARNINGS AND PRECAUTIONS (5.6, 5.10)].

5.5 Risks with Use in Pediatric Populations

Children are particularly sensitive to the respiratory depressant effects of codeine [see WARNINGS AND PRECAUTIONS (5.2, 5.3)] and promethazine [see WARNINGS AND PRECAUTIONS (5.4)]. Because of the risk of life-threatening respiratory depression and death, Promethazine with Codeine Oral Solution is contraindicated in children less than 12 years of age, and in pediatric patients younger than 18 years of age following tonsillectomy and/or adenoidectomy [see CONTRAINDICATIONS (4)].

Use of Promethazine with Codeine Oral Solution in children also exposes them to the risks of addiction, abuse, and misuse [see DRUG ABUSE AND DEPENDENCE (9)], which can lead to overdose and death [see WARNINGS AND PRECAUTIONS (5.1), OVERDOSAGE (10)]. Because the benefits of symptomatic treatment of cough associated with allergies or the common cold do not outweigh the risks of use of codeine in pediatric patients, Promethazine with Codeine Oral Solution is not indicated for use in patients younger than 18 years of age [see INDICATIONS (1), USE IN SPECIFIC POPULATIONS (8.4)].

5.6 Risks with Use in Other At-Risk Populations

Unresponsive Cough

The dosage of Promethazine with Codeine Oral Solution should not be increased if cough fails to respond; an unresponsive cough should be reevaluated in 5 days or sooner for possible underlying pathology, such as foreign body or lower respiratory tract disease [see DOSAGE AND ADMINISTRATION (2.3)].

Asthma and Other Pulmonary Disease

The use of Promethazine with Codeine Oral Solution in patients with acute or severe bronchial asthma in an unmonitored setting or in the absence of resuscitative equipment is contraindicated [seeCONTRAINDICATIONS (4)].

Opioid analgesics and antitussives, including codeine, one of the active ingredients in Promethazine with Codeine Oral Solution, should not be used in patients with acute febrile illness associated with productive cough or in patients with chronic respiratory disease where interference with ability to clear the tracheobronchial tree of secretions would have a deleterious effect on the patient's respiratory function.

Promethazine with Codeine Oral Solution-treated patients with significant chronic obstructive pulmonary disease or cor pulmonale, and those with a substantially decreased respiratory reserve, hypoxia, hypercapnia, or pre-existing respiratory depression are at increased risk of decreased respiratory drive including apnea, even at recommended dosages of Promethazine with Codeine Oral Solution [see WARNINGS AND PRECAUTIONS (5.2)].

Elderly, Cachectic, or Debilitated Patients: Life-threatening respiratory depression is more likely to occur in elderly, cachectic, or debilitated patients because they may have altered pharmacokinetics or altered clearance compared to younger, healthier patients [see WARNINGS AND PRECAUTIONS (5.2)].

Because of the risk of respiratory depression, avoid the use of opioid antitussives, including Promethazine with Codeine Oral Solution in patients with compromised respiratory function, patients at risk of respiratory failure, and in elderly, cachectic, or debilitated patients. If Promethazine with Codeine Oral Solution is prescribed, monitor such patients closely, particularly when initiating Promethazine with Codeine Oral Solution and when Promethazine with Codeine Oral Solution is given concomitantly with other drugs that depress respiration [see WARNINGS AND PRECAUTIONS (5.10)].

5.7 Risk of Accidental Overdose and Death due to Medication Errors

Dosing errors can result in accidental overdose and death. To reduce the risk of overdose and respiratory depression, ensure that the dose of Promethazine with Codeine Oral Solution is communicated clearly and dispensed accurately [see DOSAGE AND ADMINISTRATION (2.1)].

Advise patients to always use an accurate milliliter measuring device when measuring and administering Promethazine with Codeine Oral Solution. Inform patients that a household teaspoon is not an accurate measuring device and such use could lead to overdosage and serious adverse reactions [see OVERDOSAGE (10)]. For prescriptions where a measuring device is not provided, a pharmacist can provide an appropriate calibrated measuring device and can provide instructions for measuring the correct dose.

5.8 Activities Requiring Mental Alertness: Risks of Driving and Operating Machinery

Codeine and promethazine, two of the active ingredients in Promethazine with Codeine Oral Solution, may produce marked drowsiness and impair the mental and/or physical abilities required for the performance of potentially hazardous tasks such as driving a car or operating machinery. Advise patients to avoid engaging in hazardous tasks requiring mental alertness and motor coordination after ingestion of Promethazine with Codeine Oral Solution. Avoid concurrent use of Promethazine with Codeine Oral Solution with alcohol or other central nervous system depressants because additional impairment of central nervous system performance may occur [see WARNINGS AND PRECAUTIONS (5.10)].

5.9 Risks of Interactions with Drugs Affecting Cytochrome P450 Isoenzymes

The effects of concomitant use or discontinuation of cytochrome P450 3A4 inducers, 3A4 inhibitors, or 2D6 inhibitors with codeine are complex. Use of cytochrome P450 3A4 inducers, 3A4 inhibitors, or 2D6 inhibitors with Promethazine with Codeine Oral Solution requires careful consideration of the effects on the parent drug, codeine, and the active metabolite, morphine.

Cytochrome P450 3A4 Interaction

The concomitant use of Promethazine with Codeine Oral Solution with all cytochrome P450 3A4 inhibitors, such as macrolide antibiotics (e.g., erythromycin), azole-antifungal agents (e.g., ketoconazole), and protease inhibitors (e.g., ritonavir) or discontinuation of a cytochrome P450 3A4 inducer such as rifampin, carbamazepine, and phenytoin, may result in an increase in codeine plasma concentrations with subsequently greater metabolism by cytochrome P450 2D6, resulting in greater morphine levels, which could increase or prolong adverse reactions and may cause potentially fatal respiratory depression.

The concomitant use of Promethazine with Codeine Oral Solution with all cytochrome P450 3A4 inducers or discontinuation of a cytochrome P450 3A4 inhibitor may result in lower codeine levels, greater norcodeine levels, and less metabolism via 2D6 with resultant lower morphine levels. This may be associated with a decrease in efficacy, and in some patients, may result in signs and symptoms of opioid withdrawal.

Avoid the use of Promethazine with Codeine Oral Solution in patients who are taking a CYP3A4 inhibitor or CYP3A4 inducer. If concomitant use of Promethazine with Codeine Oral Solution with inhibitors and inducers of CYP3A4 is necessary, monitor patients for signs and symptoms that may reflect opioid toxicity and opioid withdrawal [see DRUG INTERACTIONS (7.1, 7.2)].

Risks of Concomitant Use or Discontinuation of Cytochrome P450 2D6 Inhibitors

The concomitant use of Promethazine with Codeine Oral Solution with all cytochrome P450 2D6 inhibitors (e.g., amiodarone, quinidine) may result in an increase in codeine plasma concentrations and a decrease in active metabolite morphine plasma concentration which could result in an analgesic efficacy reduction or symptoms of opioid withdrawal.

Discontinuation of a concomitantly used cytochrome P450 2D6 inhibitor may result in a decrease in codeine plasma concentration and an increase in active metabolite morphine plasma concentration which could increase or prolong adverse reactions and may cause potentially fatal respiratory depression.

Avoid the use of Promethazine with Codeine Oral Solution in patients who are taking a CYP2D6 inhibitor. If concomitant use of Promethazine with Codeine Oral Solution with inhibitors of CYP2D6 is necessary, monitor patients for signs and symptoms that may reflect opioid toxicity and opioid withdrawal [see DRUG INTERACTIONS (7.3)].

5.10 Risks from Concomitant Use with Benzodiazepines or other CNS Depressants

Concomitant use of opioids, including Promethazine with Codeine Oral Solution, with benzodiazepines, or other CNS depressants, including alcohol, may result in profound sedation, respiratory depression, coma, and death. Because of these risks, avoid use of opioid cough medications in patients taking benzodiazepines, other CNS depressants, or alcohol [see DRUG INTERACTIONS (7.4)].

Observational studies have demonstrated that concomitant use of opioid analgesics and benzodiazepines increases the risk of drug-related mortality compared to use of opioids alone. Because of similar pharmacologic properties, it is reasonable to expect similar risk with concomitant use of opioid cough medications and benzodiazepines, other CNS depressants, or alcohol.

Advise both patients and caregivers about the risks of respiratory depression and sedation if Promethazine with Codeine Oral Solution is used with benzodiazepines, alcohol, or other CNS depressants [see PATIENT COUNSELING INFORMATION (17)].

5.11 Risks of Use in Patients with Gastrointestinal Conditions

Promethazine with Codeine Oral Solution is contraindicated in patients with known or suspected gastrointestinal obstruction, including paralytic ileus [see CONTRAINDICATIONS (4)]. The use of codeine in Promethazine with Codeine Oral Solution may obscure the diagnosis or clinical course of patients with acute abdominal conditions.

The concurrent use of anticholinergics with Promethazine with Codeine Oral Solution may produce paralytic ileus [see DRUG INTERACTIONS (7.9)].

The codeine in Promethazine with Codeine Oral Solution may result in constipation or obstructive bowel disease, especially in patients with underlying intestinal motility disorders. Use with caution in patients with underlying intestinal motility disorders.

The codeine in Promethazine with Codeine Oral Solution may cause spasm of the sphincter of Oddi, resulting in an increase in biliary tract pressure. Opioids may cause increases in serum amylase [seeWARNINGS AND PRECAUTIONS (5.21)]. Monitor patients with biliary tract disease, including acute pancreatitis for worsening symptoms.

Administration of promethazine has been associated with reported cholestatic jaundice.

5.12 Risks of Use in Patients with Head Injury, Impaired Consciousness, Increased Intracranial Pressure, or Brain Tumors

Avoid the use of Promethazine with Codeine Oral Solution in patients with head injury, intracranial lesions, or a pre-existing increase in intracranial pressure. In patients who may be susceptible to the intracranial effects of CO2 retention (e.g., those with evidence of increased intracranial pressure or brain tumors), Promethazine with Codeine Oral Solution may reduce respiratory drive, and the resultant CO2 retention can further increase intracranial pressure. Furthermore, opioids produce adverse reactions that may obscure the clinical course of patients with head injuries.

5.13 Risk of Neuroleptic Malignant Syndrome

A potentially fatal symptom complex sometimes referred to as Neuroleptic Malignant Syndrome (NMS) has been reported in association with promethazine HCl alone or in combination with antipsychotic drugs. Clinical manifestations of NMS are hyperpyrexia, muscle rigidity, altered mental status and evidence of autonomic instability (irregular pulse or blood pressure, tachycardia, diaphoresis and cardiac dysrhythmias).

The diagnostic evaluation of patients with this syndrome is complicated. In arriving at a diagnosis, it is important to identify cases where the clinical presentation includes both serious medical illness (e.g., pneumonia, systemic infection, etc.) and untreated or inadequately treated extrapyramidal signs and symptoms (EPS). Other important considerations in the differential diagnosis include central anticholinergic toxicity, heat stroke, drug fever and primary central nervous system (CNS) pathology.

The management of NMS should include 1) immediate discontinuation of promethazine HCl, antipsychotic drugs, if any, and other drugs not essential to concurrent therapy, 2) intensive symptomatic treatment and medical monitoring, and 3) treatment of any concomitant serious medical problems for which specific treatments are available. There is no general agreement about specific pharmacological treatment regimens for uncomplicated NMS.

Since recurrences of NMS have been reported with phenothiazines, avoid use of Promethazine with Codeine Oral Solution in patients with a history consistent with NMS.

5.14 Risk of Paradoxical Reactions, including Dystonias

Promethazine with Codeine Oral Solution contains promethazine, a phenothiazine. Phenothiazines are associated with dystonic reactions, particularly in pediatric patients who have an acute illness associated with dehydration. Paradoxical reactions, including dystonia, torticollis, tongue protrusion, hyperexcitability, and abnormal movements have been reported in patients following a single administration of promethazine. Discontinue Promethazine with Codeine Oral Solution if a paradoxical reaction occurs.

5.15 Increased Risk of Seizures in Patients with Seizure Disorders

The codeine and promethazine in Promethazine with Codeine Oral Solution may increase the frequency of seizures in patients with seizure disorders, and may increase the risk of seizures occurring in other clinical settings associated with seizures. Monitor patients with a history of seizure disorders for worsened seizure control during Promethazine with Codeine Oral Solution therapy.

5.16 Co-administration with Monoamine Oxidase Inhibitors (MAOIs)

Concurrent use of Promethazine with Codeine Oral Solution is contraindicated in patients receiving monoamine oxidase inhibitors (MAOIs) or within 14 days of stopping such therapy [seeCONTRAINDICATIONS (4)]. MAOIs may potentiate the effects of morphine, codeine's active metabolite, including respiratory depression, coma, and confusion MAOIs [see DRUG INTERACTIONS (7.6)].

5.17 Bone-Marrow Depression

Promethazine with Codeine Oral Solution should be used with caution in patients with bone-marrow depression. Leukopenia and agranulocytosis have been reported, usually when promethazine has been used in association with other known marrow-toxic agents.

5.18 Severe Hypotension

Promethazine with Codeine Oral Solution may cause severe hypotension including orthostatic hypotension and syncope in ambulatory patients. There is increased risk in patients whose ability to maintain blood pressure has already been compromised by a reduced blood volume or concurrent administration of certain CNS depressant drugs (e.g., phenothiazines or general anesthetics) [see DRUG INTERACTIONS (7.4)]. Monitor these patients for signs of hypotension after initiating Promethazine with Codeine Oral Solution.

In patients with circulatory shock, Promethazine with Codeine Oral Solution may cause vasodilation that can further reduce cardiac output and blood pressure. Avoid the use of Promethazine with Codeine Oral Solution in patients with circulatory shock.

5.19 Neonatal Opioid Withdrawal Syndrome

Promethazine with Codeine Oral Solution is not recommended for use in pregnant women. Prolonged use of Promethazine with Codeine Oral Solution during pregnancy can result in withdrawal in the neonate. Neonatal opioid withdrawal syndrome, unlike opioid withdrawal syndrome in adults, may be life-threatening if not recognized and treated, and requires management according to protocols developed by neonatology experts. Observe newborns for signs of neonatal opioid withdrawal syndrome and manage accordingly. Advise pregnant women using opioids for a prolonged period of the risk of neonatal opioid withdrawal syndrome and ensure that appropriate treatment will be available. [see USE IN SPECIFIC POPULATIONS (8.1), PATIENT COUNSELING INFORMATION (17)]

5.20 Adrenal Insufficiency

Cases of adrenal insufficiency have been reported with opioid use, more often following greater than one month of use. Presentation of adrenal insufficiency may include non-specific symptoms and signs including nausea, vomiting, anorexia, fatigue, weakness, dizziness, and low blood pressure. If adrenal insufficiency is suspected, confirm the diagnosis with diagnostic testing as soon as possible. If adrenal insufficiency is diagnosed, treat with physiologic replacement doses of corticosteroids. Wean the patient off of the opioid to allow adrenal function to recover and continue corticosteroid treatment until adrenal function recovers. Other opioids may be tried as some cases reported use of a different opioid without recurrence of adrenal insufficiency. The information available does not identify any particular opioids as being more likely to be associated with adrenal insufficiency.

5.21 Drug/Laboratory Test Interactions

Because opioid agonists may increase biliary tract pressure, with resultant increase in plasma amylase or lipase levels, determination of these enzyme levels may be unreliable for 24 hours after administration of a dose of Promethazine with Codeine Oral Solution.

The following laboratory tests may be affected in patients who are receiving promethazine:

Pregnancy Tests: Diagnostic pregnancy tests based on immunological reactions between HCG and anti-HCG may result in false-negative or false-positive interpretations.

Glucose Tolerance Test: An increase in blood glucose has been reported in patients receiving promethazine.

ADVERSE REACTIONS

The following serious adverse reactions are described, or described in greater detail, in other sections:

Addiction, abuse, and misuse [see WARNINGS AND PRECAUTIONS (5.1), DRUG ABUSE AND DEPENDENCE (9.3) ]
Life-threatening respiratory depression [see WARNINGS AND PRECAUTIONS (5.2, 5.3, 5.4, 5.5, 5.6), OVERDOSAGE (10) ]
Ultra-rapid metabolism of codeine and other risk factors for life-threatening respiratory depression in children [see WARNINGS AND PRECAUTIONS (5.3) ]
Accidental overdose and death due to medication errors [see WARNINGS AND PRECAUTIONS (5.7) ]
Decreased mental alertness with impaired mental and/or physical abilities [see WARNINGS AND PRECAUTIONS (5.8) ]
Interactions with benzodiazepines and other CNS depressants [see WARNINGS AND PRECAUTIONS (5.10) ]
Paralytic ileus, gastrointestinal adverse reactions [see WARNINGS AND PRECAUTIONS (5.11)]
Increased intracranial pressure [see WARNINGS AND PRECAUTIONS (5.12) ]
Obscured clinical course in patients with head injuries [see WARNINGS AND PRECAUTIONS (5.12) ]
Neuroleptic Malignant Syndrome [see WARNINGS AND PRECAUTIONS (5.13) ]
Paradoxical reactions, including dystonias [see WARNINGS AND PRECAUTIONS (5.14) ]
Seizures [see WARNINGS AND PRECAUTIONS (5.15) ]
Interactions with MAOI [see WARNINGS AND PRECAUTIONS (5.16) ]
Bone marrow suppression [see WARNINGS AND PRECAUTIONS (5.17) ]
Severe hypotension [see WARNINGS AND PRECAUTIONS (5.18) ]
Neonatal Opioid Withdrawal Syndrome [see WARNINGS AND PRECAUTIONS (5.19) ]
Adrenal insufficiency [see WARNINGS AND PRECAUTIONS (5.20) ]

The following adverse reactions have been identified during clinical studies, in the literature, or during post-approval use of codeine and/or promethazine. Because these reactions may be reported voluntarily from a population of uncertain size, it is not always possible to reliably estimate their frequency or establish a causal relationship to drug exposure.

The most common adverse reactions to Promethazine with Codeine Oral Solution include: Sedation (somnolence, mental clouding, lethargy), impaired mental and physical performance, lightheadedness, dizziness, headache, dry mouth, nausea, vomiting, constipation, shortness of breath, sweating.

Other reactions include:

Anaphylaxis: Anaphylaxis has been reported with codeine, one of the ingredients in Promethazine with Codeine Oral Solution.

Body as a whole: Coma, death, fatigue, falling injuries, lethargy.

Cardiovascular: Peripheral edema, increased blood pressure, decreased blood pressure, tachycardia, chest pain, palpitation, syncope, orthostatic hypotension, prolonged QT interval, hot flush.

Central Nervous System: Ataxia, diplopia, facial dyskinesia, insomnia, migraine, increased intracranial pressure, seizure, tinnitus, tremor, vertigo.

Dermatologic: Flushing, hyperhidrosis, photosensitivity, pruritus, rash, urticaria.

Endocrine/Metabolic: Cases of serotonin syndrome, a potentially life-threatening condition, have been reported during concomitant use of opioids with serotonergic drugs. Cases of adrenal insufficiency have been reported with opioid use, more often following greater than one month of use. Cases of androgen deficiency have occurred with chronic use of opioids [see Clinical Pharmacology (12.2)].

Gastrointestinal: Abdominal pain, bowel obstruction, decreased appetite, diarrhea, difficulty swallowing, dry mouth, GERD, indigestion, jaundice, pancreatitis, paralytic ileus, biliary tract spasm (spasm of the sphincter of Oddi).

Genitourinary: Urinary tract infection, ureteral spasm, spasm of vesicle sphincters, urinary retention.

Hematologic: Bone marrow suppression, agranulocytosis, aplastic anemia, and thrombocytopenia have been reported.

Laboratory: Increases in serum amylase.

Musculoskeletal: Arthralgia, backache, muscle spasm.

Ophthalmic: Blurred vision, miosis (constricted pupils), visual disturbances.

Paradoxical Reactions: Dystonias, torticollis, tongue protrusion, hyperexcitability, and abnormal movements have been reported following a single administration of promethazine.

Psychiatric: Agitation, anxiety, confusion, fear, dysphoria, depression, hallucinations.

Reproductive: Hypogonadism, infertility.

Respiratory: Apnea, bronchitis, cough, dry nose, dry throat, dyspnea, nasal congestion, nasopharyngitis, respiratory depression, sinusitis, thickening of bronchial secretions, tightness of chest and wheezing, upper respiratory tract infection.

Other: Drug abuse, drug dependence, Neuroleptic Malignant Syndrome, opioid withdrawal syndrome.

DRUG INTERACTIONS

No specific drug interaction studies have been conducted with Promethazine with Codeine Oral Solution.

7.1 Inhibitors of CYP3A4

The concomitant use of Promethazine with Codeine Oral Solution with CYP3A4 inhibitors, such as macrolide antibiotics (e.g., erythromycin), azole-antifungal agents (e.g. ketoconazole), or protease inhibitors (e.g., ritonavir), may result in an increase in codeine plasma concentrations with subsequently greater metabolism by cytochrome CYP2D6, resulting in greater morphine levels, which could increase or prolong adverse reactions and may cause potentially fatal respiratory depression, particularly when an inhibitor is added after a stable dose of Promethazine with Codeine Oral Solution is achieved [see WARNINGS AND PRECAUTIONS (5.9)]. After stopping a CYP3A4 inhibitor, as the effects of the inhibitor decline, it may result in lower codeine levels, greater norcodeine levels, and less metabolism via CYP2D6 with resultant lower morphine levels [see CLINICAL PHARMACOLOGY (12.3)], resulting in decreased opioid efficacy or a withdrawal syndrome in patients who had developed physical dependence to codeine.

Avoid the use of Promethazine with Codeine Oral Solution while taking a CYP3A4 inhibitor. If concomitant use is necessary, monitor patients for respiratory depression and sedation at frequent intervals.

7.2 CYP3A4 Inducers

The concomitant use of Promethazine with Codeine Oral Solution and CYP3A4 inducers, such as rifampin, carbamazepine, or phenytoin, can result in lower codeine levels, greater norcodeine levels, and less metabolism via 2D6 with resultant lower morphine levels [see CLINICAL PHARMACOLOGY (12.3)], resulting in decreased efficacy or onset of a withdrawal syndrome in patients who have developed physical dependence [see WARNINGS AND PRECAUTIONS (5.9)]. After stopping a CYP3A4 inducer, as the effects of the inducer decline, codeine plasma concentrations may increase with subsequently greater metabolism by cytochrome CYP2D6, resulting in greater morphine levels [seeCLINICAL PHARMACOLOGY (12.3)], which could increase or prolong both the therapeutic effects and adverse reactions, and may cause serious respiratory depression.

Avoid the use of Promethazine with Codeine Oral Solution in patients who are taking CYP3A4 inducers. If concomitant use of a CYP3A4 inducer is necessary, follow the patient for reduced efficacy.

7.3 Inhibitors of CYP2D6

Codeine is metabolized by CYP2D6 to form morphine. The concomitant use of Promethazine with Codeine Oral Solution and CYP2D6 inhibitors, such as paroxetine, fluoxetine, bupropion, or quinidine, can increase the plasma concentration of codeine, but can decrease the plasma concentration of active metabolite morphine, which could result in reduced efficacy [see CLINICAL PHARMACOLOGY (12.3)].

After stopping a CYP2D6 inhibitor, as the effects of the inhibitor decline, the codeine plasma concentration will decrease but the active metabolite morphine plasma concentration will increase, which could increase or prolong adverse reactions and may cause potentially fatal respiratory depression [see CLINICAL PHARMACOLOGY (12.3)].

Avoid the use of Promethazine with Codeine Oral Solution in patients who are taking inhibitors of CYP2D6.

7.4 Benzodiazepines, and Other Depressants

Due to additive pharmacologic effect, the concomitant use of benzodiazepines or other CNS depressants, including alcohol, other sedatives/hypnotics, anxiolytics, tranquilizers, muscle relaxants, general anesthetics, antipsychotics, and other opioids, can increase the risk of hypotension, respiratory depression, profound sedation, coma, and death. Avoid the use of Promethazine with Codeine Oral Solution in patients who are taking benzodiazepines or other CNS depressants. [see WARNINGS AND PRECAUTIONS (5.10)].

7.5 Serotonergic Drugs

The concomitant use of opioids with other drugs that affect the serotonergic neurotransmitter system has resulted in serotonin syndrome. If concomitant use is warranted, carefully observe the patient, particularly during treatment initiation. Discontinue Promethazine with Codeine Oral Solution if serotonin syndrome is suspected.

7.6 Monoamine Oxidase Inhibitors (MAOIs)

Promethazine with Codeine Oral Solution is contraindicated in patients who are taking MAOIs (i.e., certain drugs used for depression, psychiatric or emotional conditions, or Parkinson's disease) or have taken MAOIs within 14 days [see CONTRAINDICATIONS (4)].

MAOI interactions with opioids may manifest as serotonin syndrome or opioid toxicity (e.g., respiratory depression, coma) [see WARNINGS AND PRECAUTIONS (5.16)].

Drug interactions, including an increased incidence of extrapyramidal effects, have been reported when some MAOI and phenothiazines are used concomitantly.

7.7 Muscle Relaxants

Codeine may enhance the neuromuscular blocking action of skeletal muscle relaxants and produce an increased degree of respiratory depression. Avoid the use of Promethazine with Codeine Oral Solution in patients taking muscle relaxants. If concomitant use is necessary, monitor patients for signs of respiratory depression that may be greater than otherwise expected.

7.8 Diuretics

Opioids can reduce the efficacy of diuretics by inducing the release of antidiuretic hormone. Monitor patients for signs of diminished diuresis and/or effects on blood pressure and increase the dosage of the diuretic as needed.

7.9 Anticholinergic Drugs

The concomitant use of anticholinergic drugs with Promethazine with Codeine Oral Solution may increase risk of urinary retention and/or severe constipation, which may lead to paralytic ileus [seeWARNINGS AND PRECAUTIONS (5.11)]. Monitor patients for signs of urinary retention or reduced gastric motility when Promethazine with Codeine Oral Solution is used concomitantly with anticholinergic drugs.

Additive adverse effects resulting from cholinergic blockade (e.g., xerostomia, blurred vision, or constipation) may occur when anticholinergic drugs are administered with promethazine].

OVERDOSAGE

Clinical Presentation

Codeine

Acute overdose with codeine is characterized by respiratory depression (a decrease in respiratory rate and/or tidal volume, Cheyne-Stokes respiration, cyanosis), extreme somnolence progressing to stupor or coma, skeletal muscle flaccidity, cold and clammy skin, constricted pupils, and, in some cases, pulmonary edema, bradycardia, partial or complete airway obstruction, atypical snoring, hypotension, circulatory collapse, cardiac arrest, and death.

Codeine may cause miosis, even in total darkness. Pinpoint pupils are a sign of opioid overdose but are not pathognomonic (e.g., pontine lesions of hemorrhagic or ischemic origin may produce similar findings). Marked mydriasis rather than miosis may be seen with hypoxia in overdose situations [seeCLINICAL PHARMACOLOGY (12.2)].

Promethazine

Signs and symptoms of overdosage with promethazine range from mild depression of the central nervous system and cardiovascular system to profound hypotension, respiratory depression, unconsciousness and sudden death. Other reported reactions include hyperreflexia, hypertonia, ataxia, athetosis and extensor-plantar reflexes (Babinski reflex).

Stimulation may be evident, especially in children and geriatric patients. Convulsions may rarely occur. A paradoxical reaction has been reported in children receiving single doses of 75 mg to 125 mg orally, characterized by hyperexcitability and nightmares.

Atropine-like signs and symptoms (dry mouth, fixed dilated pupils, flushing, tachycardia, hallucinations, gastrointestinal symptoms, convulsions, urinary retention, cardiac arrhythmias and coma) may be observed.

Impaired secretion from sweat glands following toxic doses of drugs with anticholinergic side effects may predispose to hyperthermia.

Treatment of Overdose

Treatment of overdosage is driven by the overall clinical presentation, and consists of discontinuation of Promethazine with Codeine Oral Solution together with institution of appropriate therapy. Give primary attention to the reestablishment of adequate respiratory exchange through provision of a patent and protected airway and the institution of assisted or controlled ventilation. Employ other supportive measures (including oxygen and vasopressors) in the management of circulatory shock and pulmonary edema as indicated. Cardiac arrest or arrhythmias will require advanced life-support techniques. Gastric emptying may be useful in removing unabsorbed drug.

The opioid antagonists, naloxone and nalmefene, are specific antidotes for respiratory depression resulting from opioid overdose. For clinically significant respiratory or circulatory depression secondary to codeine overdose, administer an opioid antagonist. An antagonist should not be administered in the absence of clinically significant respiratory depression. Because the duration of opioid reversal is expected to be less than the duration of action of codeine in Promethazine with Codeine Oral Solution, carefully monitor the patient until spontaneous respiration is reliably reestablished. If the response to an opioid antagonist is suboptimal or only brief in nature, administer additional antagonist as directed by the product's prescribing information. The respiratory depressant effects of promethazine are not reversed by opioid antagonists, such as naloxone.

Because of the potential for promethazine to reverse epinephrine's vasopressor effect, epinephrine should NOT be used to treat hypotension associated with promethazine overdose.

Hemodialysis is not routinely used to enhance the elimination of codeine or promethazine from the body.

DESCRIPTION

Promethazine with Codeine Oral Solution contains codeine, an opioid agonist, and promethazine, a phenothiazine.

Each 5 mL of Promethazine with Codeine Oral Solution contains 10 mg of codeine phosphate and 6.25 mg of promethazine hydrochloride for oral administration.

Promethazine with Codeine Oral Solution has a pH between 4.8 and 5.4 and contains alcohol 7%.

Promethazine with Codeine Oral Solution also contains the following inactive ingredients: artificial and natural flavors, citric acid, D&C Red 33, FD&C Blue 1, FD&C Yellow 6, glycerin, saccharin sodium, sodium benzoate, sodium citrate, sodium propionate, water, and other ingredients.

Codeine Phosphate

The chemical name for codeine phosphate is 7,8-Didehydro-4, 5α-epoxy-3-methoxy-17-methylmorphinan-6α-ol phosphate (1:1) (salt) hemihydrate. Codeine is one of the naturally occurring phenanthrene alkaloids of opium derived from the opium poppy, it is classified pharmacologically as a narcotic analgesic. The phosphate salt of codeine occurs as white, needle-shaped crystals or white crystalline powder. Codeine phosphate is freely soluble in water and slightly soluble in alcohol. The molecular weight is 406.37. Its molecular formula is C18H21NO3•H3PO4 • ½ H2O, and it has the following chemical structure.

Promethazine Hydrochloride

The chemical name for promethazine hydrochloride, a phenothiazine derivative, is (±)-10-[2-(Dimethylamino)propyl] phenothiazine monohydrochloride. Promethazine hydrochloride occurs as a white to faint yellow, practically odorless, crystalline powder which slowly oxidizes and turns blue on prolonged exposure to air. It is soluble in water and freely soluble in alcohol. The molecular weight is 320.88. Its molecular formula is C17H20N2S•HCl, and it has the following chemical structure.

CLINICAL PHARMACOLOGY

12.4 Mechanism of Action

Codeine

Codeine is an opioid agonist relatively selective for the mu-opioid receptor, but with a much weaker affinity than morphine. The analgesic and antitussive properties of codeine have been speculated to come from its conversion to morphine. The precise mechanism of action of codeine and other opiates is not known; however, codeine is believed to act centrally on the cough center. In excessive doses, codeine will depress respiration.

Promethazine

Promethazine is a phenothiazine derivative, which differs structurally from the antipsychotic phenothiazines by the presence of a branched side chain and no ring substitution. Promethazine possesses antihistamine (H1 receptor antagonist), antiemetic, sedative, and anticholinergic effects. It prevents released histamine from dilating capillaries and causing edema of the respiratory mucosa.

12.5 Pharmacodynamics

Codeine

Effects on the Central Nervous System

Codeine produces respiratory depression by direct action on brain stem respiratory centers. The respiratory depression involves a reduction in the responsiveness of the brain stem respiratory centers to both increases in carbon dioxide tension and to electrical stimulation.

Codeine causes miosis, even in total darkness. Pinpoint pupils are a sign of opioid overdose but are not pathognomonic (e.g., pontine lesions of hemorrhagic or ischemic origins may produce similar findings). Marked mydriasis rather than miosis may be seen due to hypoxia in overdose situations.

Effects on the Gastrointestinal Tract and Other Smooth Muscle

Codeine causes a reduction in motility associated with an increase in smooth muscle tone in the antrum of the stomach and duodenum. Digestion of food in the small intestine is delayed and propulsive contractions are decreased. Propulsive peristaltic waves in the colon are decreased, while tone may be increased to the point of spasm resulting in constipation. Other opioid-induced effects may include a reduction in biliary and pancreatic secretions, spasm of sphincter of Oddi, and transient elevations in serum amylase.

Effects on the Cardiovascular System

Codeine produces peripheral vasodilation which may result in orthostatic hypotension or syncope. Manifestations of histamine release and/or peripheral vasodilation may include pruritus, flushing, red eyes and sweating and/or orthostatic hypotension.

Effects on the Endocrine System

Opioids inhibit the secretion of adrenocorticotropic hormone (ACTH), cortisol, and luteinizing hormone (LH) in humans [see ADVERSE REACTIONS (6)]. They also stimulate prolactin, growth hormone (GH) secretion, and pancreatic secretion of insulin and glucagon.

Chronic use of opioids may influence the hypothalamic-pituitary-gonadal axis, leading to androgen deficiency that may manifest as low libido, impotence, erectile dysfunction, amenorrhea, or infertility. The causal role of opioids in the clinical syndrome of hypogonadism is unknown because the various medical, physical, lifestyle, and psychological stressors that may influence gonadal hormone levels have not been adequately controlled for in studies conducted to date [see ADVERSE REACTIONS (6)].

Effects on the Immune System

Opioids have been shown to have a variety of effects on components of the immune system in in vitro and animal models. The clinical significance of these findings is unknown. Overall, the effects of opioids appear to be modestly immunosuppressive.

Concentration–Adverse Reaction Relationships

There is a relationship between increasing codeine plasma concentration and increasing frequency of dose-related opioid adverse reactions such as nausea, vomiting, CNS effects, and respiratory depression. In opioid-tolerant patients, the situation may be altered by the development of tolerance to opioid-related adverse reactions.

Promethazine

Promethazine competitively antagonize H1 receptors located in most of the smooth muscle including the gastrointestinal tract, uterus, large blood vessels and bronchial muscle. Actions of histamine on H1receptors increases capillary permeability and edema formation, flare and pruritus.

12.6 Pharmacokinetics

Absorption

Codeine is absorbed from the gastrointestinal tract with maximum plasma concentration occurring 60 minutes post administration. The presence of a high-fat, high-calorie meal did not significantly impact the PK of codeine.

Promethazine is well absorbed from the gastrointestinal tract. Clinical effects are apparent within 20 minutes after oral administration and generally last four to six hours, although they may persist as long as 12 hours.

Distribution

Codeine has been reported to have an apparent volume of distribution of approximately 3 to 6 L/kg, indicating extensive distribution of the drug into tissues. Codeine has low plasma protein binding with about 7 to 25% of codeine bound to plasma proteins. Codeine passes the blood brain barrier and the placental barrier. Small amounts of codeine and its metabolite, morphine, are transferred to human breast milk.

Promethazine is widely distributed in body tissues. Promethazine has high protein binding with about 80 to 93% of promethazine bound to plasma proteins. Promethazine passes the blood brain barrier and the placental barrier.

Elimination

Metabolism

Codeine is metabolized by conjugation with glucuronic acid to codeine-6-glucuronide (about 70 to 80%), by O-demethylation to morphine (about 5 to 10%), and by N-demethylation to norcodeine (about 10%). UDP-glucuronosyltransferase (UGT) 2B7 and 2B4 are the major enzymes mediating glucuronidation of codeine to C6G. Cytochrome P450 2D6 is the major enzyme responsible for conversion of codeine to morphine and P450 3A4 is the major enzyme mediating conversion of codeine to norcodeine. Morphine and norcodeine are further metabolized by conjugation with glucuronic acid. The glucuronide metabolites of morphine are morphine-3-glucuronide (M3G) and morphine-6-glucuronide (M6G). Morphine and its M6 glucuronide conjugate are pharmacologically active. Whether C6G has pharmacological activity is unknown. Norcodeine and M3 glucuronide conjugate of morphine are generally not considered to be pharmacologically active.

Promethazine is metabolized by the liver to a variety of inactive metabolites such as sulfoxides of promethazine, N-demethylpromethazine and other glucuronides.

Excretion

Approximately 90% of the total dose of codeine is excreted through the kidneys, of which approximately 10% is unchanged codeine. Plasma half-lives of codeine and its metabolites have been reported to be approximately 3 hours.

Promethazine has an elimination half-life of 10-14 hours, with excretion of metabolites appearing in the urine and feces. The sulfoxides of promethazine and N-demethylpromethazine are the predominant metabolites appearing in the urine.

NONCLINICAL TOXICOLOGY

13.3 Carcinogenesis, Mutagenesis, Impairment of Fertility

Carcinogenicity, mutagenicity, and fertility studies have not been conducted with Promethazine with Codeine Oral Solution; however, published information is available for the individual active ingredients.

Codeine

Carcinogenicity studies were conducted with codeine. Two-year studies in F344/N rats and B6C3F1 mice were conducted to assess the carcinogenic potential of codeine. No evidence of tumorigenicity was observed in male and female rats at codeine dietary doses up to 70 and 80 mg/kg/day (approximately equivalent to 15 and 20 times, the MRHD on a mg/m2 basis, respectively). No evidence of tumorigenicity was observed in male and female mice at codeine dietary doses up to 400 mg/kg/day (approximately equivalent to 45 times the MRHD on a mg/m2 basis).

Codeine was not mutagenic in the in vitro bacterial reverse mutation assay or clastogenic in the in vitro Chinese hamster ovary (CHO) cell chromosomal aberration assay.

Fertility studies with codeine have not been conducted.

Promethazine

Carcinogenicity studies were conducted with promethazine hydrochloride. Two-year studies in F344/N rats and B6C3F1 mice were conducted to assess the carcinogenic potential of promethazine hydrochloride. No evidence of tumorigenicity was observed in male and female rats at promethazine hydrochloride oral doses up to 33 mg/kg/day for 5 days/week (approximately equivalent to 10 times the MRHD on a mg/m2 basis). No evidence of tumorigenicity was observed in male and female mice at promethazine hydrochloride oral doses up to 45 and 15 mg/kg/day for 5 days/week (approximately equivalent to 7 and 2 times the MRHD on a mg/m2 basis, respectively).

Promethazine hydrochloride was not mutagenic in the in vitro bacterial reverse mutation assay or clastogenic in the in vitro Chinese hamster ovary (CHO) cell chromosomal aberration assay.

Fertility studies with promethazine have not been conducted

PATIENT COUNSELING INFORMATION

Advise the patient to read the FDA-approved patient labeling (Medication Guide).